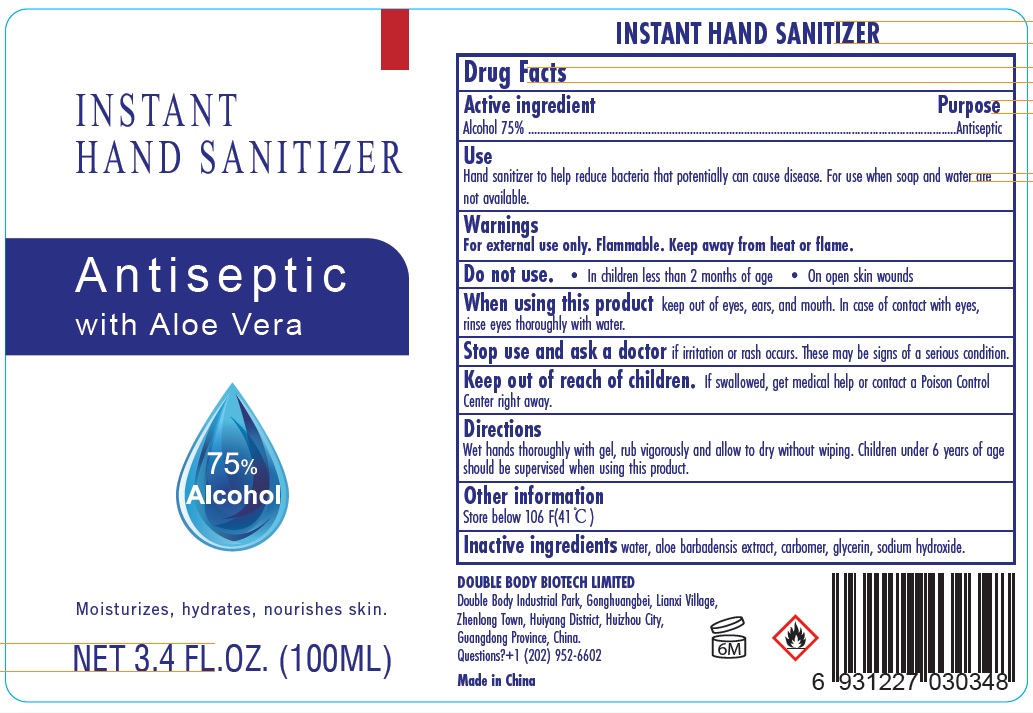 DRUG LABEL: INSTANT HAND SANITIZER
NDC: 74657-002 | Form: GEL
Manufacturer: Double Body Biotech Limited
Category: otc | Type: HUMAN OTC DRUG LABEL
Date: 20200618

ACTIVE INGREDIENTS: ALCOHOL 75 mL/100 mL
INACTIVE INGREDIENTS: WATER; ALOE VERA LEAF; SODIUM HYDROXIDE; GLYCERIN; CARBOMER HOMOPOLYMER, UNSPECIFIED TYPE

Active ingredient

Alcohol 75%

Purpose

Antiseptic

Use

Hand sanitizer to help reduce bacteria that potentially can cause disease. For use when soap and water are not available.

Warnings

For external use only. Flammable. Keep away from heat or flame.

Do not use.

- In children less than 2 months of age
- On open skin wounds

When using this product keep out of eyes, ears, and mouth. In case of contact with eyes, rinse eyes thoroughly with water.

Keep out of reach of children. If swallowed, get medical help or contact a Poison Control Center right away.

Stop use and ask a doctor if irritation or rash occurs. These may be signs of a serious condition.

Directions

Wet hands thoroughly with gel, rub vigorously and allow to dry without wiping, Children under 6 years of age should be supervised when using this product.

Other information

Store below 106F 41C

Inactive ingredients

water

aloe barbadensis extract

carbomer

glycerin

sodium hydroxide